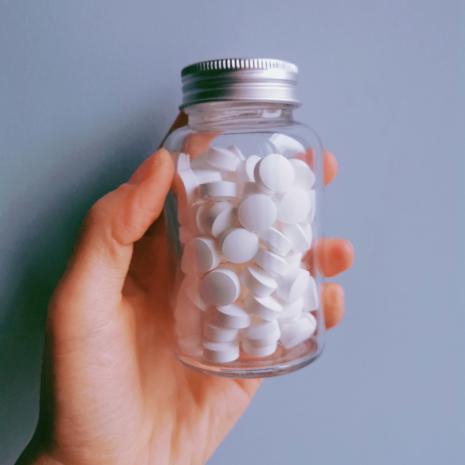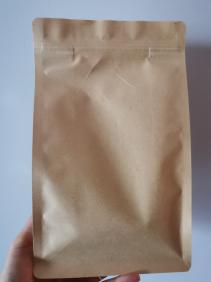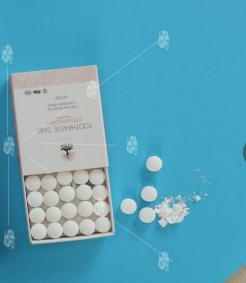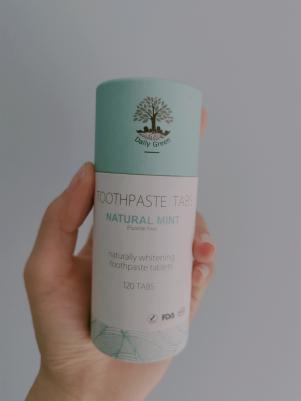 DRUG LABEL: Fluoride
NDC: 80143-001 | Form: TABLET, CHEWABLE
Manufacturer: Henan Dailygreen Trade Co.,Ltd.
Category: otc | Type: HUMAN OTC DRUG LABEL
Date: 20211219

ACTIVE INGREDIENTS: SODIUM FLUORIDE 0.00145 1/1 1
INACTIVE INGREDIENTS: XYLITOL 0.51012 1/1 1; OLEIC ACID 0.005 1/1 1; SODIUM BICARBONATE 0.03 1/1 1; CALCIUM CARBONATE 0.05 1/1 1; SODIUM ISETHIONATE 0.3 1/1 1; ERYTHRITOL 0.03 1/1 1; RACEMENTHOL 0.00343 1/1 1; CELLULOSE, MICROCRYSTALLINE 0.06 1/1 1; MYRCENE 0.01 1/1 1

Fluoride Toothpaste Tablets

Active ingredient

Sodium Fluoride 0.145%

Purpose

Anticaries

Uses

Aids in the prevention of dental cavities

Warnings

˙ Keep out of reach of children under 6 years of age.

˙ If more than used for brushing is accidentally swallowed, get medical help or contact a Poison Control Center right away.

Keep out of reach of children under 6 years of age.

Directions

1. Chew: Place tablet in mouth and chew for 5 seconds.
2. Hydrate: Use a wet brush to moisten the toothpaste in your mouth and brush teeth.

3. Brush: Brush for at least 30 seconds. Rinse and spit out thoroughly. Brush teeth, preferably after each meal or at least twice a day, or as directed by a dentist or doctor. Instruct children under 12 years of age in good brushing and rinsing habits (to minimize swallowing). Supervise children as necessary until capable of using without supervision. Children under 6 years of age: Do not use unless directed by a dentist or doctor.

Other Information

Store in room temperature. Avoid direct sunlight.

Shelf life: 3 years.

Production Date: as shown in the packing

Website: www.dailygreen.en.alibaba.com

Inactive Ingredients

Microcrystalline Cellulose, Xylitol, Erythritol, Natural Mint Flavor, Calcium Carbonate, SodiumCocoyl Isethionate, Sodium Bicarbonate, Laurel Extract, Cooling Oil

PACKAGE LABEL

60 tablets / glass bottle: NDC: 80143-001-01

62 tablets / glass bottle: NDC: 80143-001-02

120 tablets / glass bottle: NDC: 80143-001-03

PACKAGE LABEL

60 tablets / paper tube: NDC: 80143-001-04

90 tablets / paper tube: NDC: 80143-001-05

120 tablets / paper tube: NDC: 80143-001-06

PACKAGE LABEL

30 tablets / carton: NDC: 80143-001-07

60 tablets / carton: NDC: 80143-001-08

PACKAGE LABEL

2 tablets / bag: NDC: 80143-001-09

62 tablets / bag: NDC: 80143-001-10

120 tablets / bag: NDC: 80143-001-11

1000 tablets / bag: NDC: 80143-001-12